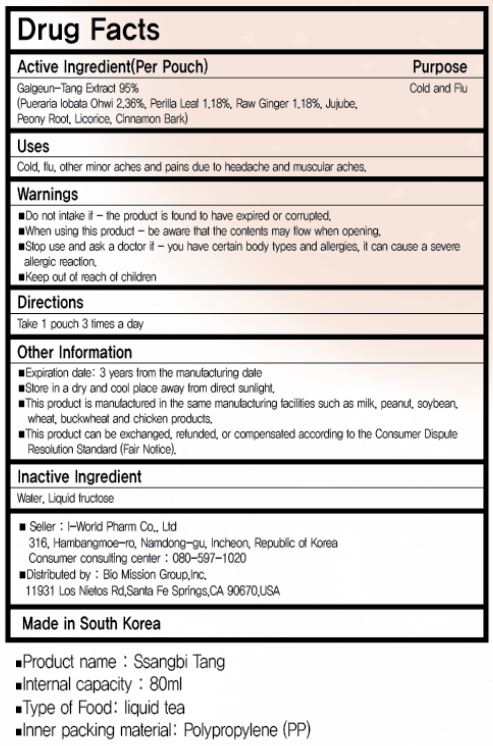 DRUG LABEL: SSANGBI TANG
NDC: 73442-0008 | Form: LIQUID
Manufacturer: I World Pharmaceutical Co., Ltd.
Category: otc | Type: HUMAN OTC DRUG LABEL
Date: 20250212

ACTIVE INGREDIENTS: GINGER 1.121 g/100 mL; PERILLA FRUTESCENS LEAF 1.121 g/100 mL; PUERARIA MONTANA VAR. LOBATA WHOLE 2.242 g/100 mL
INACTIVE INGREDIENTS: FRUCTOSE; WATER

ACTIVE INGREDIENT

galgeun-tang extract (pueraria lobata ohwi, perilla leaf, raw ginger, jujube, peony root, licorice, cinnamon bark)

PURPOSE

cold, flu, other minor aches and pains due to headache and muscular aches

Keep out of reach of children

INDICATIONS AND USAGE

take 1 pouch 3 times a day

WARNINGS

do not intake if the product is found to have expired or corrupted

when using this product be aware that the contents may flow when opening

stop use and ask a doctor if you have certain body types and allergies, it can cause a severe allergic reaction

INACTIVE INGREDIENT

water, liquid fructose

DOSAGE AND ADMINISTRATION

For oral use only